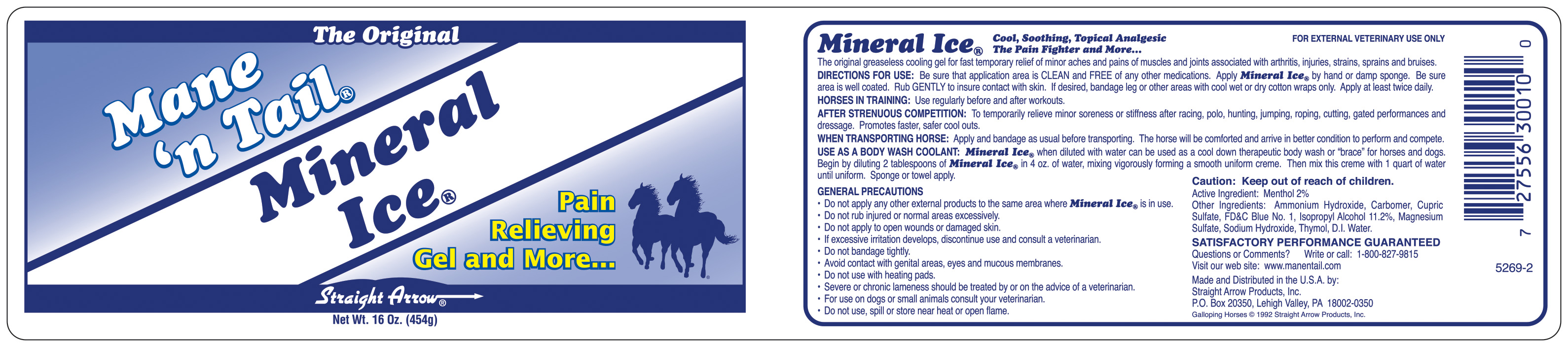 DRUG LABEL: Mineral Ice
								
NDC: 62001-0300 | Form: GEL
Manufacturer: Straight Arrow Products, Inc.
Category: animal | Type: OTC ANIMAL DRUG LABEL
Date: 20250707

ACTIVE INGREDIENTS: MENTHOL .02 g/1 g

The Original Mane 'n Tail Mineral Ice Pain Relieving Gel and More...

Active Ingredient:

Menthol 2%

GENERAL PRECAUTIONS

- Do not apply any other external products to the same area where Mineral Ice is in use.
- Do not rub injured or normal areas excessively.
- Do not apply to open wounds or damaged skin.
- If excessive irritation develops, discontinue use and consult a veterinarian.
- Do not bandage tightly
- Avoid contact with genital areas, eyes and mucous membranes.
- Do not use with heating pads.
- Severe or chronic lameness should be treated by or on the advice of a veterinarian.
- For use on dogs or small animals consult your veterinarian.
- Do not use, spill or store near heat or open flame

Caution: Keep out of reach of children

INDICATIONS AND USAGE

DIRECTIONS FOR USE:

Be sure that application area is CLEAN and FREE of any other medications. Apply Mineral Ice by hand or damp sponge. Be sure area is well coated. Rub GENTLY to insure contact with skin. If desired, bandage leg or other areas with cool wet or dry cotton wraps only. Apply at least twice daily.
HORSES IN TRAINING:

Use regularly before and after workouts.
AFTER STRENUOUS COMPETITION:

To temporarily relieve minor soreness or stiffness after racing, polo, hunting, jumping, roping, cutting, gated performances and dressage. Promotes faster, safer cool outs.
WHEN TRANSPORTING A HORSE:

Apply and bandage as usual before transporting. The horse will be comforted and arrive in better condition to perform and compete.
USE AS A BODY WASH COOLANT:

Mineral Ice when diluted with water can be used as a cool down therapeutic body wash or "brace" for horses and dogs. Begin by diluting 2 tablespoons of Mineral Ice in 4 oz. of water, mixing vigorously forming a smooth uniform creme. Then mix this creme with 1 quart of water until uniform. Sponge or towel apply.

INACTIVE INGREDIENT

Other Ingredients:Ammonium Hydroxide, Carbomer, Cupric Sulfate, FD and C Blue No. 1, Isopropyl Alcohol 11.2%, Magnesium Sulfate, Sodium Hydroxide, Thymol, D.I. Water.

Questions or Comments? Write or Call: 1-800-827-9815
Visit our web site: www.manentail.com
Made and Distributed in the U.S.A. by: Straight Arrow Products, Inc.
P.O. Box 20350, Lehigh Valley, PA 18002-0350